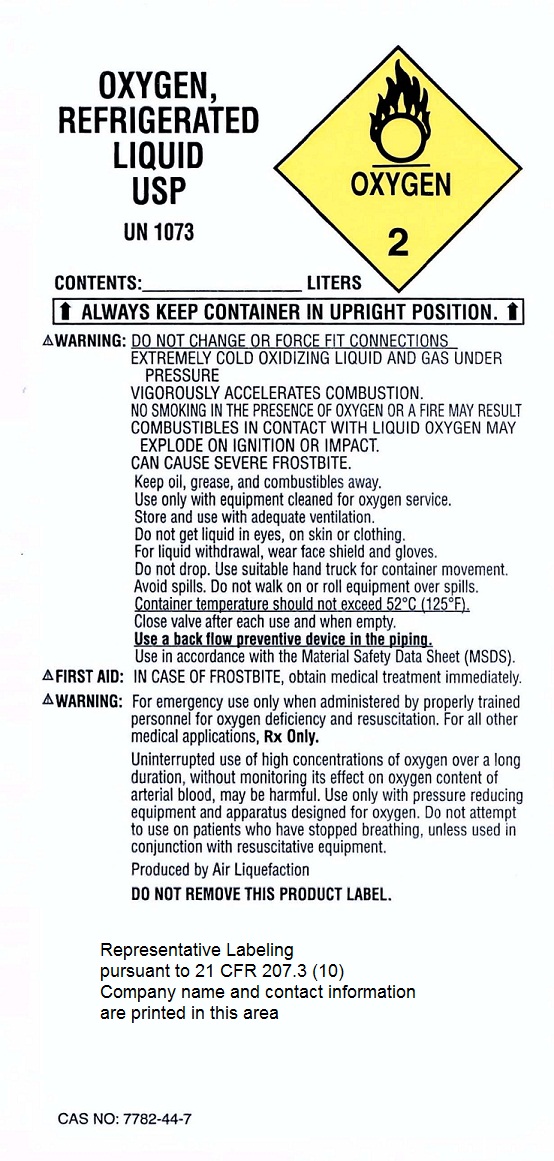 DRUG LABEL: Oxygen
NDC: 52726-4083 | Form: GAS
Manufacturer: CHI National Home Care dba MercyOne Des Moines Home Respiratory Care
Category: prescription | Type: HUMAN PRESCRIPTION DRUG LABEL
Date: 20191216

ACTIVE INGREDIENTS: OXYGEN 99 L/100 L

Oxygen

Principal for Oxygen Product

OXYGEN,

REFRIGERATED LIQUID

USP

UN 1073

CONTENTS: LITERS

ALWAYS KEEP CONTAINER IN UPRIGHT POSITION

WARNING:

DO NOT CHANGE OR FORCE FIT CONNECTIONS

EXTREMELY COLD OXIDIZING LIQUID AND GAS UNDER PRESSURE

VIGOROUSLY ACCELERATES COMBUSTION

NO SMOKING IN THE PRESENCE OF OXYGEN OR A FIRE MAY RESULT

COMBUSTIBLES IN CONTACT WITH LIQUID OXYGEN MAY EXPLODE

ON IGNITION OR IMPACT.

CAN CAUSE SEVERE FROSTBITE.

Keep oil, grease, and combustibles away.

Use only with equipment cleaned for oxygen service.

Store and use with adequate ventilation.

Do not get liquid in eyes, on skin or clothing.

For liquid withdrawal, wear face shield and gloves.

Do not drop. Use suitable hand truck for container movement.

Container temperatures should not exceed 52 degrees C (125 degrees F).

Close valve after each use and when empty.

Use a back flow preventive device in the piping.

Use in accordance with the Material Safety Data Sheet (MSDS).

FIRST AID:
IN CASE OF FROSTBITE, obtain medical treatment immediately.
WARNING:
For emergency use only when administered by properly trained
personnel for oxygen deficiency and resuscitation. For all other
medical applications, Rx only.
Uninterrupted use of high concentrations of oxygen over a long
duration, without monitoring its effect on oxygen content of arterial
blood, may be harmful. Use only with pressure reducing equipment
and apparatus designed for oxygen. Do not attempt to use on
patients who have stopped breathing, unless used in conjunction
with resuscitative equipment.
Produced by Air Liquefaction
DO NOT REMOVE THIS PRODUCT LABEL.